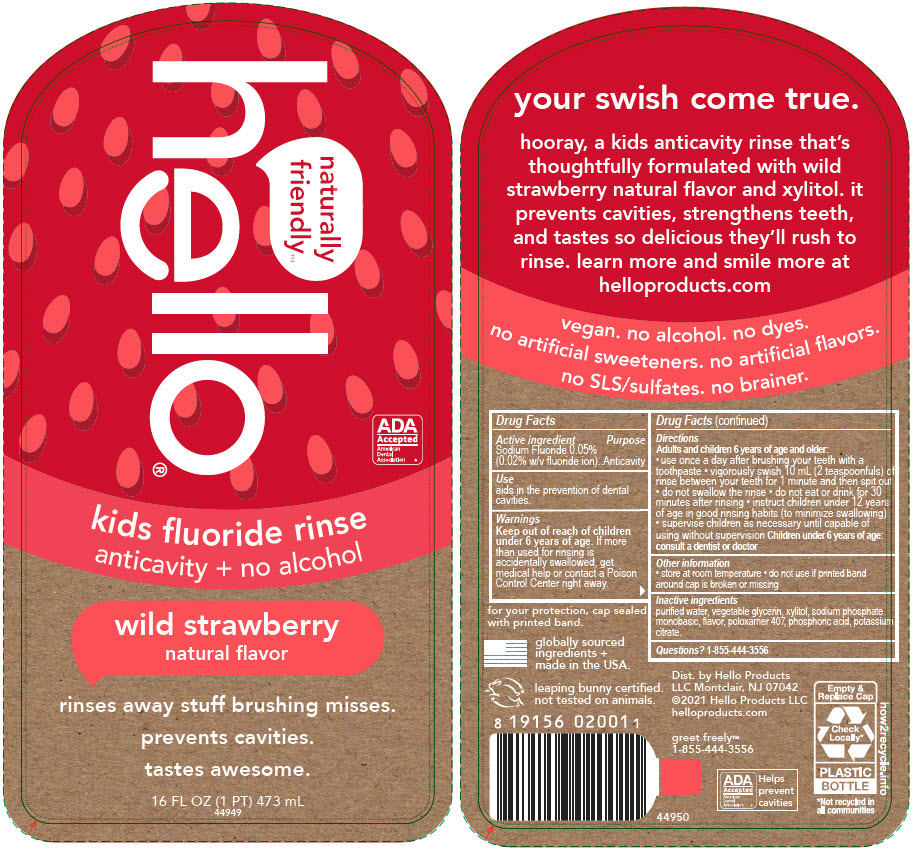 DRUG LABEL: Hello Wild Strawberry
NDC: 35000-685 | Form: MOUTHWASH
Manufacturer: Colgate-Palmolive Company
Category: otc | Type: HUMAN OTC DRUG LABEL
Date: 20250217

ACTIVE INGREDIENTS: SODIUM FLUORIDE 0.02 g/100 mL
INACTIVE INGREDIENTS: WATER; GLYCERIN; XYLITOL; SODIUM PHOSPHATE, MONOBASIC, ANHYDROUS; POLOXAMER 407; PHOSPHORIC ACID; POTASSIUM CITRATE

Hello® Wild Strawberry

Drug Facts

Active ingredient

Sodium Fluoride 0.05% (0.02% w/v fluoride ion)

Purpose

Anticavity

Use

aids in the prevention of dental cavities.

Warnings

Keep out of reach of children under 6 years of age. If more than used for rinsing is accidentally swallowed, get medical help or contact a Poison Control Center right away.

Directions

Adults and children 6 years of age and older:

- use once a day after brushing your teeth with a toothpaste
- vigorously swish 10 mL (2 teaspoonfuls) of rinse between your teeth for 1 minute and then spit out
- do not swallow the rinse
- do not eat or drink for 30 minutes after rinsing
- instruct children under 12 years of age in good rinsing habits (to minimize swallowing)
- supervise children as necessary until capable of using without supervision Children under 6 years of age: consult a dentist or doctor

Other information

- store at room temperature
- do not use if printed band around cap is broken or missing

Inactive ingredients

purified water, vegetable glycerin, xylitol, sodium phosphate monobasic, flavor, poloxamer 407, phosphoric acid, potassium citrate.

Questions?

1-855-444-3556

Dist. by Hello Products
LLC Montclair, NJ 07042

PRINCIPAL DISPLAY PANEL - 473 mL Bottle Label

naturally
friendly™
hello®

ADA
Accepted
American
Dental
Association ®

kids fluoride rinse
anticavity + no alcohol

wild strawberry
natural flavor

rinses away stuff brushing misses.

prevents cavities.

tastes awesome.

16 FL OZ (1 PT) 473 mL

44949